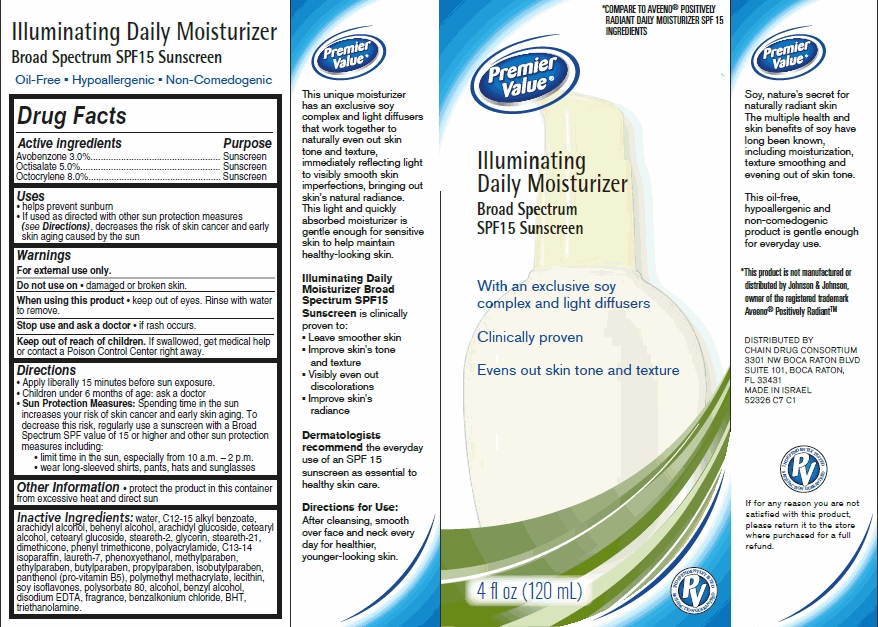 DRUG LABEL: Premier Value Illuminating Daily Moisturizer
NDC: 68016-523 | Form: CREAM
Manufacturer: Chain Drug Consortium, LLC
Category: otc | Type: HUMAN OTC DRUG LABEL
Date: 20121210

ACTIVE INGREDIENTS: AVOBENZONE 3 g/100 mL; OCTOCRYLENE 8 g/100 mL; OCTISALATE 5 g/100 mL
INACTIVE INGREDIENTS: WATER; GLYCERIN; DIMETHICONE; PHENOXYETHANOL; BENZYL ALCOHOL; EDETATE DISODIUM; ALKYL (C12-15) BENZOATE; ARACHIDYL ALCOHOL; DOCOSANOL; ARACHIDYL GLUCOSIDE; CETOSTEARYL ALCOHOL; STEARETH-2; STEARETH-21; PHENYL TRIMETHICONE; POLYACRYLAMIDE (10000 MW); C13-14 ISOPARAFFIN; LAURETH-7; METHYLPARABEN; ETHYLPARABEN; BUTYLPARABEN; PROPYLPARABEN; ISOBUTYLPARABEN; PANTHENOL; LECITHIN, SOYBEAN; SOY ISOFLAVONES; POLYSORBATE 80; CETEARYL GLUCOSIDE; BENZALKONIUM CHLORIDE; TROLAMINE; BUTYLATED HYDROXYTOLUENE

Premier Value® Illuminating Daily Moisturizer

Active ingredient

Avobenzone 3.0%

Octisalate 5.0%

Octocrylene 10.0%

Purpose

Sunscreen

Keep Out of Reach of Children

If swallowed, get medical help or contact a Poison Control Center right away.

Uses

help prevent sunburn

If used as directed with other sun protection measures (see Directions), decreases the risk of skin cancer and early skin aging caused by the sun

Warnings

For external use only.

Do not use on damaged or broken skin.

When using this product keep out of eyes. Rinse with water to remove.

Stop use and ask a doctor if rash occurs.

Directions

Apply liberally 15 minutes before sun exposure.

Children under 6 months of age: ask a doctor

Sun Protection Measures: Spending time in the sun increases your risk of skin cancer and early skin aging. To decrease this risk, regularly use a sunscreen with a Broad Spectrum SPF value of 15 or higher and other sun protection measures including:

limit time in the sun, especially from 10 a.m.-2 p.m.

wear long-sleeved shirts, pants, hats and sunglasses

Inactive ingredients

water, C12-15 alkyl benzoate, arachidyl alcohol, behenyl alcohol, arachidyl glucoside, cetearyl alcohol, cetearyl glucoside, steareth-2, glycerin, steareth-21, dimethicone, cetearyl alcohol, phenyl trimethicone, polyacrylamide, C13-14 isoparaffin, laureth-7, phenoxyethanol, methylparaben, ethylparaben, butylparaben, propylparaben, isobutylparaben, panthenol (pro-vitamin B5), polymethyl methacrylate, lecithin, soy isoflavones, polysorbate 80, alcohol, benzyl alcohol, disodium EDTA, fragrance, benzalkonium chloride, BHT, triethanolamine

Package/Label Principal Display Panel

Premier Value® Illuminating Daily Moisturizer
Broad Spectrum SPF15 Sunscreen

With an exclusive soy complex and light diffusers

Clinically proven

Evens out skin tone and texture

4 FL OZ (120 mL)

DISTRIBUTED BY:
CHAIN DRUG CONSORTIUM
3301 NW BOCA RATON BLVD
SUITE 101, BOCA RATON,

FL 33431
MADE IN ISRAEL
52326 C7 C1

Carton Label